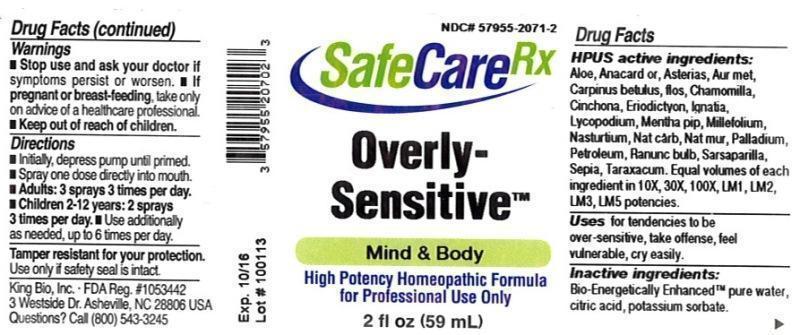 DRUG LABEL: Overly Sensitive
NDC: 57955-2071 | Form: LIQUID
Manufacturer: King Bio Inc.
Category: homeopathic | Type: HUMAN OTC DRUG LABEL
Date: 20131223

ACTIVE INGREDIENTS: ALOE 10 [hp_X]/59 mL; SEMECARPUS ANACARDIUM JUICE 10 [hp_X]/59 mL; ASTERIAS RUBENS 10 [hp_X]/59 mL; GOLD 10 [hp_X]/59 mL; CARPINUS BETULUS FLOWERING TOP 10 [hp_X]/59 mL; MATRICARIA RECUTITA 10 [hp_X]/59 mL; CINCHONA OFFICINALIS BARK 10 [hp_X]/59 mL; ERIODICTYON CALIFORNICUM LEAF 10 [hp_X]/59 mL; STRYCHNOS IGNATII SEED 10 [hp_X]/59 mL; LYCOPODIUM CLAVATUM SPORE 10 [hp_X]/59 mL; MENTHA PIPERITA 10 [hp_X]/59 mL; ACHILLEA MILLEFOLIUM 10 [hp_X]/59 mL; NASTURTIUM OFFICINALE 10 [hp_X]/59 mL; SODIUM CARBONATE 10 [hp_X]/59 mL; SODIUM CHLORIDE 10 [hp_X]/59 mL; PALLADIUM 10 [hp_X]/59 mL; KEROSENE 10 [hp_X]/59 mL; RANUNCULUS BULBOSUS 10 [hp_X]/59 mL; SMILAX REGELII ROOT 10 [hp_X]/59 mL; SEPIA OFFICINALIS JUICE 10 [hp_X]/59 mL; TARAXACUM OFFICINALE 10 [hp_X]/59 mL
INACTIVE INGREDIENTS: WATER; CITRIC ACID MONOHYDRATE; POTASSIUM SORBATE

Overly-Sensitive™

ACTIVE INGREDIENT

HPUS active ingredients: Aloe socotrina, Anacardium orientale, Asterias rubens, Aurum metallicum, Carpinus betulus, flos, Chamomilla, Cinchona officinalis, Eriodictyon californicum, Ignatia amara, Lycopodium clavatum, Mentha piperita, Millefolium, Nasturtium aquaticum, Natrum carbonicum, Natrum muriaticum, Palladium metallicum, Petroleum, Ranunculus bulbasus, Sarsaparilla, Sepia, Taraxacum officinale. Equal volumes of each ingredient in 10X, 30X, 100X, LM1, LM2, LM3, LM5 potencies.

INDICATIONS AND USAGE

Uses for tendencies to be over-sensitive, take offense, feel vulnerable, cry easily.

INACTIVE INGREDIENT

Inactive Ingredients: Bio-Energetically Enhanced™ pure water, citric acid and potassium sorbate.

Warnings

- Stop use and ask a docter if symptoms persist or worsen.
- If pregnant or breast-feeding, take only on advice of a healthcare professional.

- Keep out of reach of children.

Directions

- Initially, depress pump until primed.
- Spray one dose directly into mouth.
- Adults: 3 sprays 3 times per day.
- Children 2-12 years: 2 sprays 3 times per day.
- Use additionally as needed, up to 6 times per day.

OTHER SAFETY INFORMATION

Tamper resistant for your protection. Use only if safety seal is intact.

PURPOSE

Uses for tendencies to be:

- over-sensitive
- take offense
- feel vulnerable
- cry easily